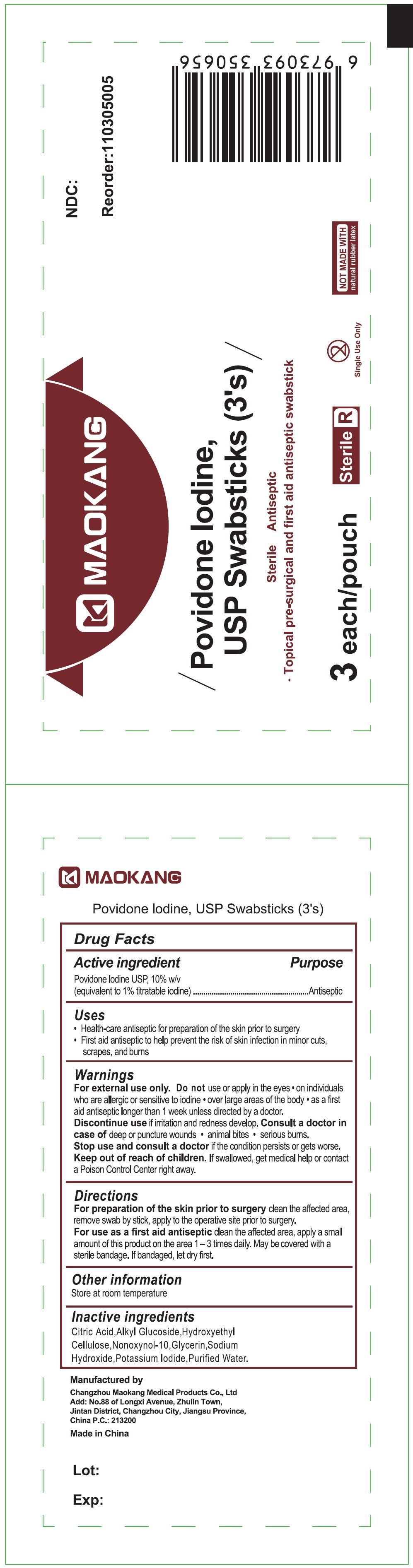 DRUG LABEL: Maokang Povidone Iodine Swabsticks 3s
NDC: 59050-271 | Form: SOLUTION
Manufacturer: Changzhou Maokang Medical Products Co.,Ltd
Category: otc | Type: HUMAN OTC DRUG LABEL
Date: 20231114

ACTIVE INGREDIENTS: POVIDONE-IODINE 100 mg/1 mL
INACTIVE INGREDIENTS: CITRIC ACID MONOHYDRATE; HYDROXYMETHYL CELLULOSE; NONOXYNOL-10; GLYCERIN; SODIUM HYDROXIDE; POTASSIUM IODIDE; WATER

Maokang Povidone Iodine Swabsticks

Active ingredient

Povidone lodine USP, 10% w/v (equivalent to 1% titratable iodine)

Purpose

Antiseptic

Uses

• Health-care antiseptic for preparation of the skin prior to surgery.

• First aid antiseptic to help prevent the risk of skin infection in minor cuts, scrapes, and burns

Warnings

For external use only.

Do not

use or apply in the eyes • on individuals who are allergic or sensitive to idonie • over large areas of the body • as a first aid antispetic longer than 1 week unless directed by a doctor.

Discontinue use if irritation and redness develop.

Consult a doctor in case of

deep or puncture wounds • animal bites • serious burns.

Stop use and consult a doctor

if the condition persists or gets worse.

Keep out of reach of children

If swallowed, get medical help or contact a Poison Control Center right away.

Directions

For preparation of the skin prior to surgeryclean the affected area, remove swab by stick, apply to the operative site prior to surgery.

For use as a first aid antispetic clean the affected area, apply a small amount of this product on the area 1 - 3 times daily. May be covered with a sterile bandage. if bandaged, let dry first.

Other information

Store at room temparature

Inactive ingredients

Citric Acid, Alkyl Glucoside, Hydroxyethyl Cellulose, Nonoxynol-10, Glycerin, Sodium Hydroxide, Potassium lodide, Purified Water.